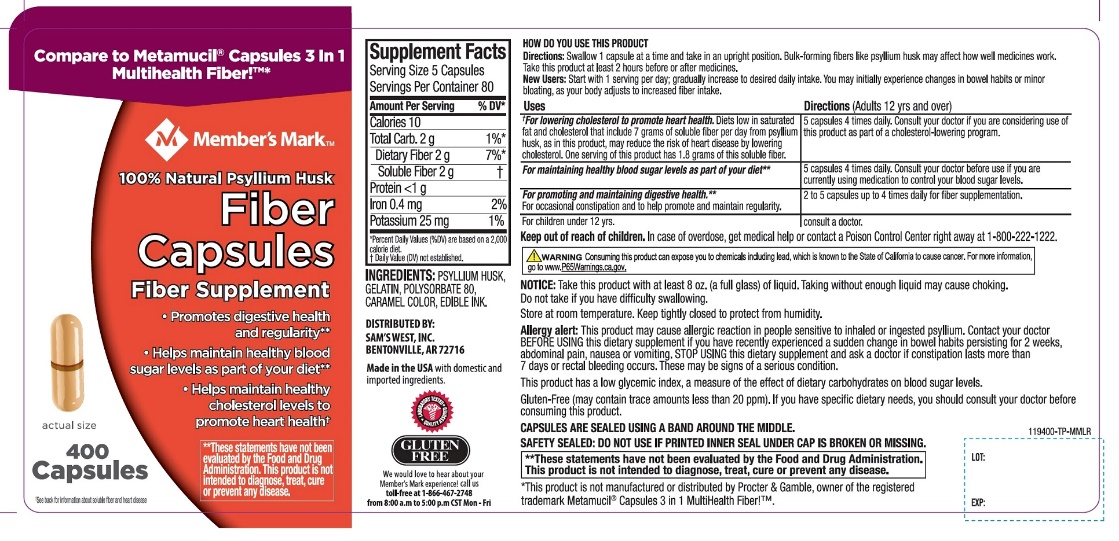 DRUG LABEL: SAMS WEST
NDC: 68196-119 | Form: CAPSULE
Manufacturer: SAM'S WEST INC
Category: otc | Type: HUMAN OTC DRUG LABEL
Date: 20251120

ACTIVE INGREDIENTS: PSYLLIUM HUSK 0.52 g/1 1
INACTIVE INGREDIENTS: CARAMEL; GELATIN, UNSPECIFIED; POLYSORBATE 80

Fiber Capsules Psyllium Husk 400 Capsules

Drug Facts

Active ingredient (in each capsule)

Psyllium husk approximately 0.52 g

Purpose

Fiber Laxative

Uses

- effective in treating occasional constipation and restoring regularity

Warnings

Choking

Taking this product without adequate fluid may cause it to swell and block your throat or esophagus and may cause choking. Do not take this product if you have difficulty in swallowing. If you experience chest pain, vomiting, or difficulty in swallowing or breathing after taking this product, seek immediate medical attention.

Allergy alert

This product may cause allergic reaction in people sensitive to inhaled or ingested psyllium.

Ask a doctor before use if you have

- a sudden change in bowel habits persisting for 2 weeks
- abdominal pain, nausea or vomiting

Stop use and ask a doctor if

- constipation lasts more than 7 days
- rectal bleeding occurs

These may be signs of a serious condition.

Keep out of reach of children

In case of overdose, get medical help or contact a Poison Control Center right away at 1-800-222-1222.

Directions

- Take this product with at least 8 ounces (a full glass) of water or other fluid. Taking this product without enough liquid may cause choking. See choking warning.
- Adults 12 years and older:5 capsules with at least 8 oz. of liquid (swallow 1 capsule at a time) at the first sign of irregularity. Can be taken up to 3 times daily. Generally produces effect in 12-72 hours.
- children 12 years and under:Ask a doctor
- Laxatives, including bulk fibers, may affect how well other medicines work. If you are taking a prescription medication by mouth, take this product at least 2 hours before or 2 hours after the prescribed medicine.
- As your body adjusts to increased fiber intake, you may experience changes in bowel habits or minor bloating.

Other information

- each capsule contains: potassium 5 mg
- capsules are sealed using a band around the middle
- store at room temperature tightly closed to protect from humidity
- contains a 100% natural, therapeutic fiber
- tamper evident: do not use if printed inner seal under cap is broken or missing

Inactive ingredients

caramel color, edible ink, gelatin, polysorbate 80

Questions or comments?

1-866-467-2748

PRINCIPAL DISPLAY PANEL - 400 Capsules

NDC 68196-119-40

Member’s Mark®

QUALITY GUARANTEED

Compare to the Metamucil®MultiHealth Capsules®active ingredient*

100% natural psyllium fiber

Fiber capsules

Fiber supplement laxative for regularity

- Helps maintain blood sugar levels as part of your diet**
- Helps lower cholesterol to promote heart health††
- Promotes digestive health**

GLUTEN FREE

400 CAPSULES

LABORATORY TESTED

QUALITY ASSURED

††See back for information about soluble fiber and heart disease

**THESE STAEMENTS HAVE NOT BEEN EVALUATED BY FOOD AND DRUG ADMINSTRATION, THIS PRODUCT IS NOT INTEDED TO DIAGNOSE, TREAT, CURE OR PREVENT ANY DISEASE

GLUTEN FREE (If you have specific dietary needs, you should dietary needs; you should consult your doctor before consuming this product. This product has a low glycemic index, a measure of the effect of dietary carbohydrates on blood sugar levels.)

DISTRIBUTED BY: SAM’S WEST, INC.

BENTONVILLE, AR 72716

For comments or suggestions, call us toll-free at 1-866-467-2748 from 8:00 a.m. to 5:00 p.m. CST Mon-Fri

*This product is not manufactured or distributed by Procter & Gamble, the distributor of Metamucil®Capsules.